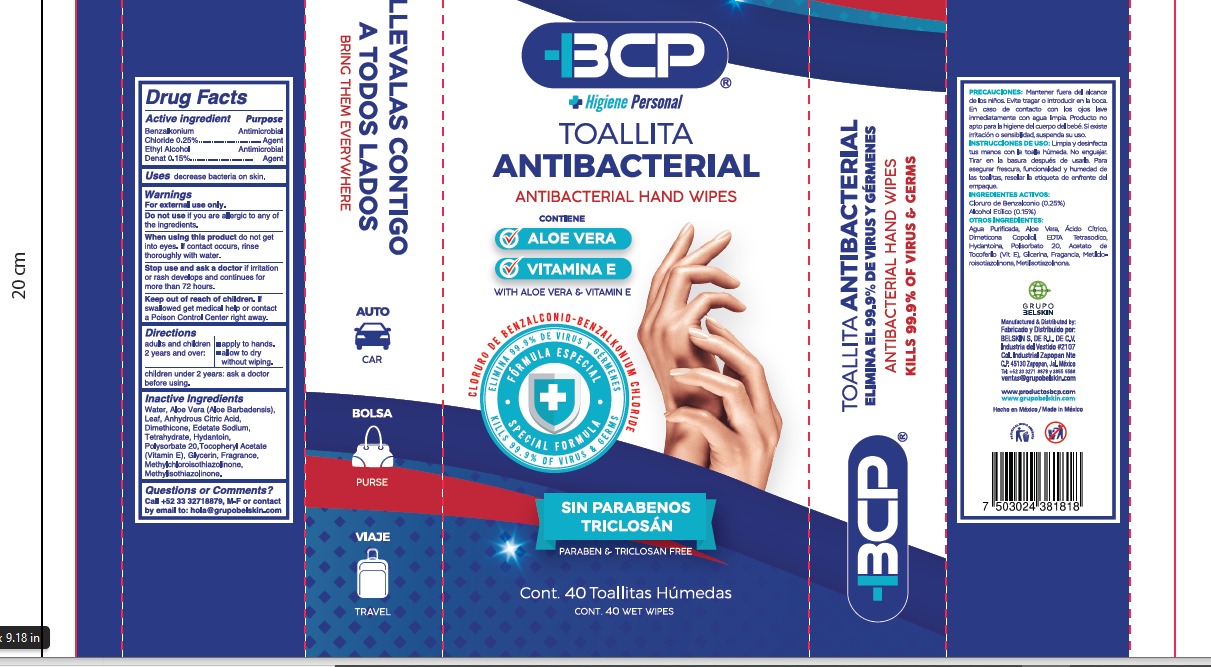 DRUG LABEL: BCP
NDC: 78502-7000 | Form: CLOTH
Manufacturer: BELSKIN S. DE, R.L. DE C.V
Category: otc | Type: HUMAN OTC DRUG LABEL
Date: 20200729

ACTIVE INGREDIENTS: ALCOHOL 5 g/100 g; BENZALKONIUM CHLORIDE 0.25 g/100 g
INACTIVE INGREDIENTS: ALOE VERA LEAF 0.05 g/100 g; .ALPHA.-TOCOPHEROL ACETATE, D- 0.08 g/100 g; POLYSORBATE 20 0.005 g/100 g; WATER 93.885 g/100 g; METHYLCHLOROISOTHIAZOLINONE 0.1 g/100 g; METHYLISOTHIAZOLINONE 0.1 g/100 g; EDETATE SODIUM TETRAHYDRATE 0.008 g/100 g; HYDANTOIN 0.002 g/100 g; ANHYDROUS CITRIC ACID 0.015 g/100 g; GLYCERIN 0.5 g/100 g; DIMETHICONE 0.005 g/100 g

ANTISEPTIC WET WIPES

ACTIVE INGREDIENTS

Benzalkonium chloride

Ethyl Alcohol

INACTIVE INGREDIENTS

WATER, ALOE VERA LEAF, ANHYDROUS CITRIC ACID, DIMETHICONE, GLYCERIN, EDETATE SODIUM TETRAHYDRATE, ALPHA TOCOPHEROL ACETATE, HYDANTOIN, POLYSORBATE 20, METHYLCHLOROISOTHIAZOLINONE, METHYLISOTHIAZOLINONE

WARNINGS AND PRECAUTIONS

Children under 6 years of age should be supervised when using.

If swallowed, get medical help or contact a Poison Control Center right away.

WARNINGS

For external use only. Flammable. Keep away from heat or flame

DOSAGE AND ADMINISTRATION

APPLY TO HANDS AND ALLOW TO DRY WITHOUT WIPING.

PURPOSE

ANTIBACTERIAL

STOP USE

STOP USE AND ASK A DOCTOR IF IRRITATION OR RASH DEVELOPS AND CONTINUES FOR MORE THAN 72 HOURS.

KEEP OUT OF REACH OF CHILDREN

INDICATIONS AND USAGE

APPLY TO HANDS AND ALLOW TO DRY WITHOUT WIPING.